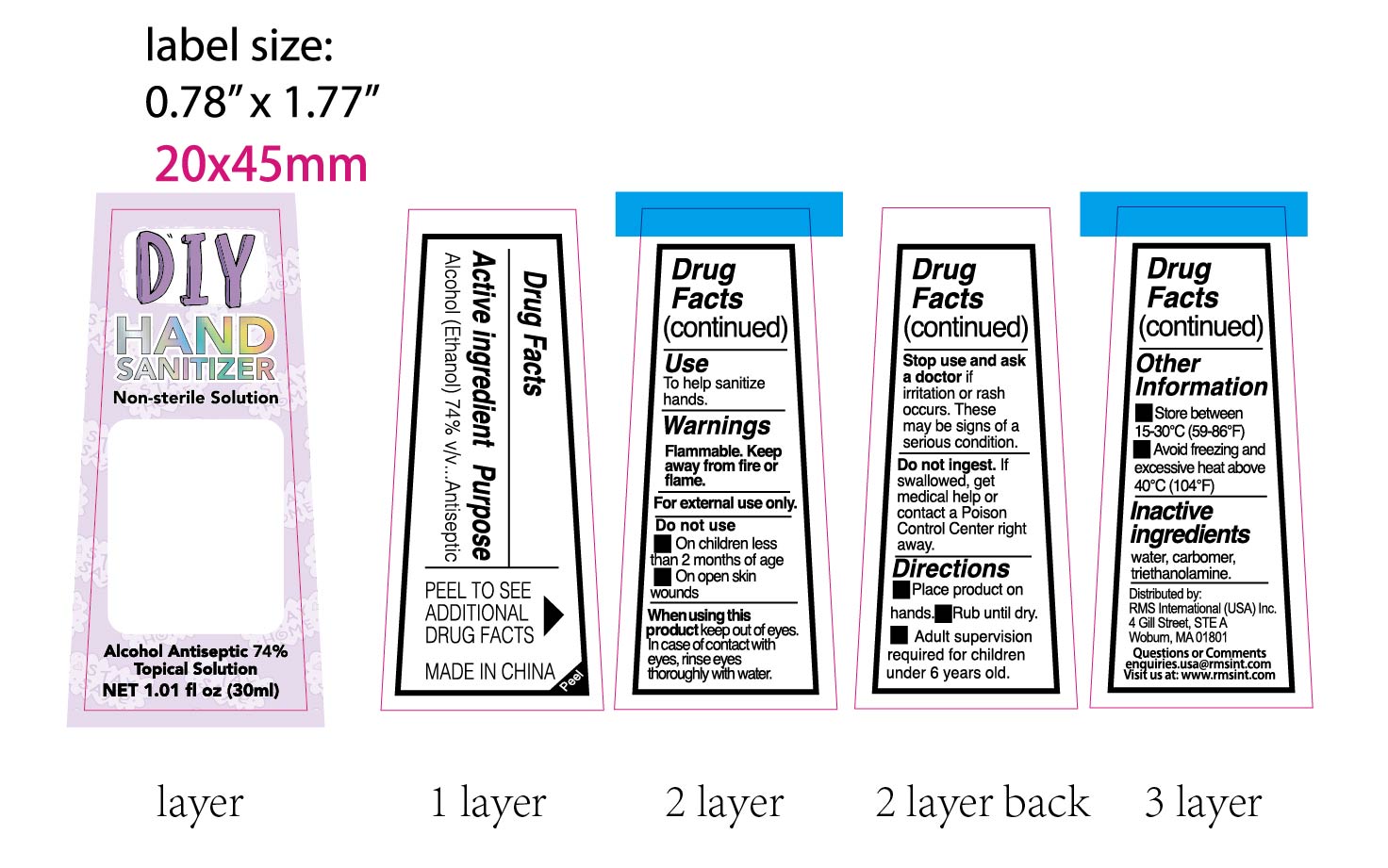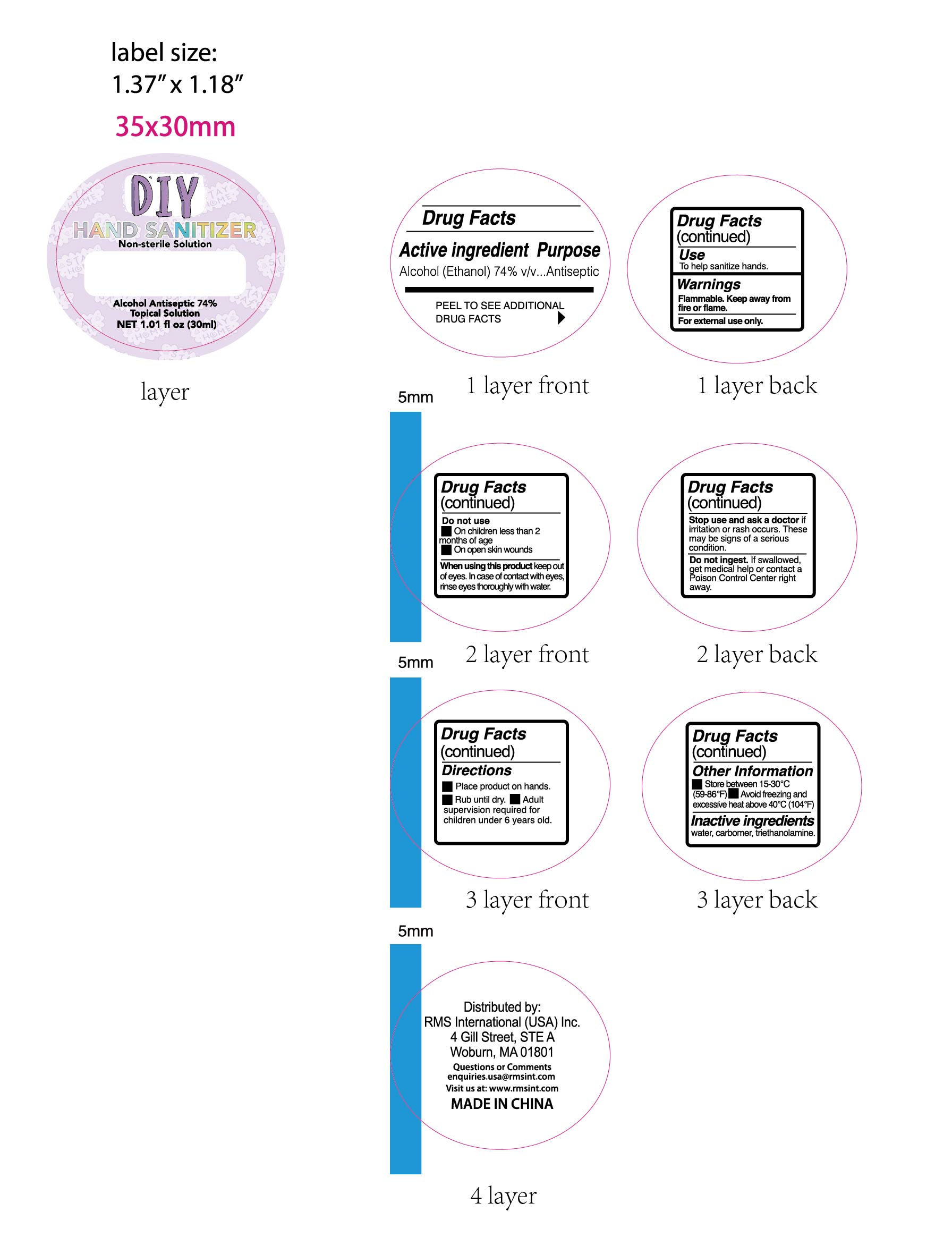 DRUG LABEL: HAND SANITIZER
NDC: 74440-009 | Form: GEL
Manufacturer: Jiangxi Iris Chemical Co.,Ltd
Category: otc | Type: HUMAN OTC DRUG LABEL
Date: 20200706

ACTIVE INGREDIENTS: ALCOHOL 74 mL/100 mL
INACTIVE INGREDIENTS: TROLAMINE; WATER; CARBOMER HOMOPOLYMER, UNSPECIFIED TYPE

HAND SANITIZER

Active ingredient[s]

Alcohol(Ethanol)74%V/v.

Purpose

Antiseptic

Use[s]

To help sanitize hands

Warnings

Flammable. Keep away from fire or flame
For external use only.

Do not use

on children less than 2 months of age

on open skin wounds

When using this product

keep out of eyes,ears, and mouth.In case of contact with eyes,rinse eyes thoroughly with water.

Stop use and ask a doctor

if irritation or rash occurs.These may be signs of a serious condition.

Keep out of reach of children

If swallowed, get medical help or contact a Poison Control Center right away.

Directions

Place product on hands
Rub until dry.
Adut supervision required for children under 6 years old.

Other information

Store between 15-30°C(59-86°F)
Avoid freezing andexcessive heat above40°C(104°F)

Inactive ingredients

Water, Carbomer,Triethanolamine.